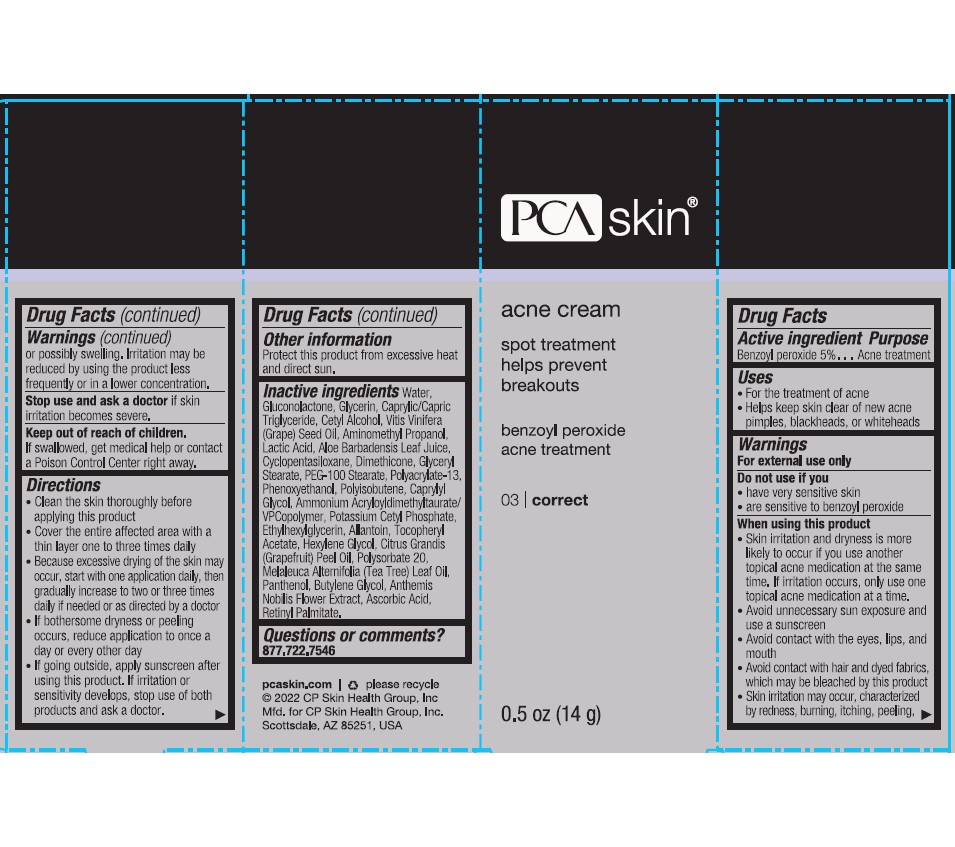 DRUG LABEL: PCA SKIN Acne
NDC: 68726-169 | Form: CREAM
Manufacturer: CP Skin Health Group, Inc.
Category: otc | Type: HUMAN OTC DRUG LABEL
Date: 20241203

ACTIVE INGREDIENTS: BENZOYL PEROXIDE 5 g/100 g
INACTIVE INGREDIENTS: ALOE VERA LEAF; WATER; GLYCERIN; ALLANTOIN; PANTHENOL; PHENOXYETHANOL; HEXYLENE GLYCOL; CAPRYLYL GLYCOL; POLYSORBATE 20; BUTYLENE GLYCOL; GLUCONOLACTONE; CETYL ALCOHOL; GRAPE; AMINOMETHYLPROPANOL; LACTIC ACID; CITRUS PARADISI SEED; TEA TREE OIL; CHAMAEMELUM NOBILE FLOWER; GLYCERYL MONOSTEARATE; POLYOXYL 100 STEARATE; DIMETHICONE; CYCLOMETHICONE 5; ASCORBIC ACID; .ALPHA.-TOCOPHEROL ACETATE, D-; VITAMIN A PALMITATE; ETHYLHEXYLGLYCERIN; POTASSIUM CETYL PHOSPHATE

PCA Skin Acne Cream

ACTIVE INGREDIENT: Benzoyl Peroxide (5.0%)

Purpose: Acne Treatment

USES:

- Treats existing and helps prevent new acne blemishes/blackheads.

WARNINGS:

- When using this product, avoid unnecessary sun exposure and use a sunscreen.
- For external use only
- Using other topical acne drugs at the same time or immediately following the use of this product may increase dryness or irritation of the skin. If this occurs, only one drug should be used unless directed by a physician.
- Do not use in or near the eyes.

Keep out of reach of children. If swallowed, get medical help or contact a Poison Control Center Immediately.

DOSAGE AND ADMINISTRATION

DIRECTIONS: Cleanse skin thoroughly before applying. Apply a small amount of cream to areas where pimples occur. Do not rinse. Start with one acne treatment every other day and gradually increase to once daily or as directed by a physician. If going outside, use a sunscreen. Allow Acne Cream to dry, then follow sunscreen label directions. If irritation develops or sensitivity develops, discontinue use of both products and consult a physician.

INACTIVE INGREDIENT

Other Ingredients: Water/Aqua/Eau, Gluconolactone, Glycerin, Caprylic/Capric Triglyceride, Cetyl Alcohol, Vitis Vinifera (Grape) Seed Oil, Aminomethyl Propanol, Lactic Acid, Aloe Barbadensis Leaf Juice, Cyclopentasiloxane, Dimethicone, Glyceryl Stearate, PEG-100 Stearate, Melaleuca Arternifolia (Tea Tree) Leaf Oil, Tocopheryl Acetate, Ascorbic Acid, Retinyl Palmitate, Anthemis Nobilis Flower Extract, Citrus Grandis (Grapefruit) Peel Oil, Allantoin, Panthenol, Polyacrylate-13, Polyisobutene, Caprylyl Glycol, Ammonium Acryloyldimethyltaurate/VP Copolymer, Potassium Cetyl Phosphate, Ethylhexylglycerin, Hexylene Glycol, Polysorbate 20, Butylene Glycol, Phenoxyethanol.